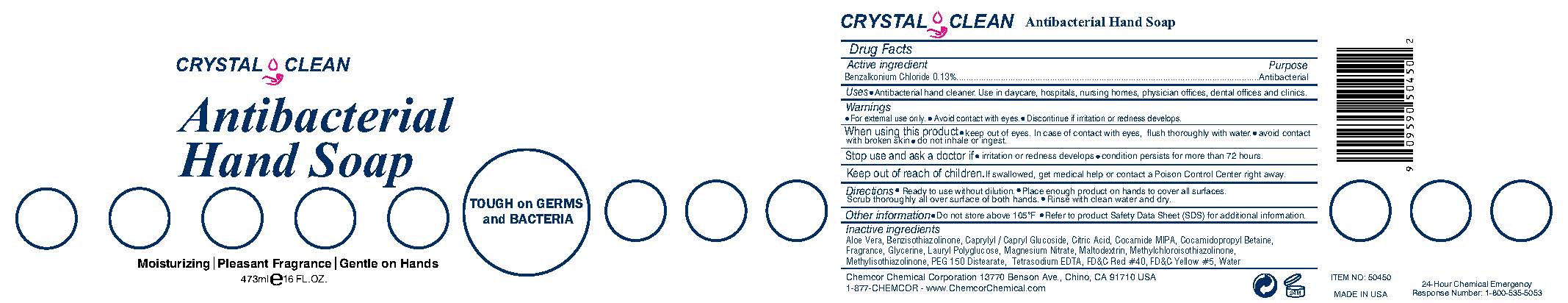 DRUG LABEL: Crystal Clean Antibacterial HandSoap
NDC: 68041-740 | Form: LIQUID
Manufacturer: Chemcor Chemical Corporation
Category: otc | Type: HUMAN OTC DRUG LABEL
Date: 20251222

ACTIVE INGREDIENTS: BENZALKONIUM CHLORIDE .13 g/1 mL
INACTIVE INGREDIENTS: ALOE VERA LEAF; CAPRYLYL/CAPRYL OLIGOGLUCOSIDE; ANHYDROUS CITRIC ACID; COCO MONOISOPROPANOLAMIDE; COCAMIDOPROPYL BETAINE; GLYCERIN; LAURYL GLUCOSIDE; MAGNESIUM NITRATE; MALTODEXTRIN; METHYLCHLOROISOTHIAZOLINONE; METHYLISOTHIAZOLINONE; PEG-150 DISTEARATE; FD&C RED NO. 40; EDETATE SODIUM; WATER; FD&C YELLOW NO. 5

CRYSTAL CLEAN Antibacterial Hand Soap

Active ingredient

Benzalkonium Chloride .13%

Purpose

Antibacterial

INDICATIONS AND USAGE

Uses • Antibacterial hand cleaner. Use in daycare, hospitals, nursing homes, physician offices, dental offices and clinics.

Warnings

•For external use only. • Avoid contact with eyes. • Discontinue if irritation or redness develops.

When using this product • keep out of eyes. In case of contact with eyes, flush thoroughly with water. • avoid contact with broken skin • do not inhale or ingest.

Stop use and ask a doctor if • irritation or redness develops • condition persists for more than 72 hours.

Keep out of reach of children. If swallowed, get medical help or contact a Poison Control Center right away

DOSAGE AND ADMINISTRATION

Directions • Ready to use without dilution. • Place enough product on hands to cover all surfaces. Scrub thoroughly all over surface of both hands. • Rinse with clean water and dry.

Inactive ingredients

Aloe Barbadensis Leaf Juice, Caprylyl/Capryl Glucoside, Citric Acid, Cocamide MIPA, Cocamidopropyl Betaine, Fragrance, Glycerin, Lauryl Polyglucose, Magnesium Nitrate, Maltodextrin, Methylchloroisothiazolinone, Methylisothiazolinone, PEG 150 Distearate, FD&C Red #40, Tetrasodium EDTA, Water, FD&C Yellow #5

TOUGH on GERMS and BACTERIA

Moisturizing | Pleasant Fragrance | Gentle on Hands

May be harmful if swallowed. May cause irritation to eyes.

Chemcor Chemical Corporation 13770 Benson Ave., Chino, CA 91710 USA

1-877-CHEMCOR - www.ChemcorChemical.com

MADE IN USA

24-Hour Chemical Emergency

Response Number: 1-800-535-5053